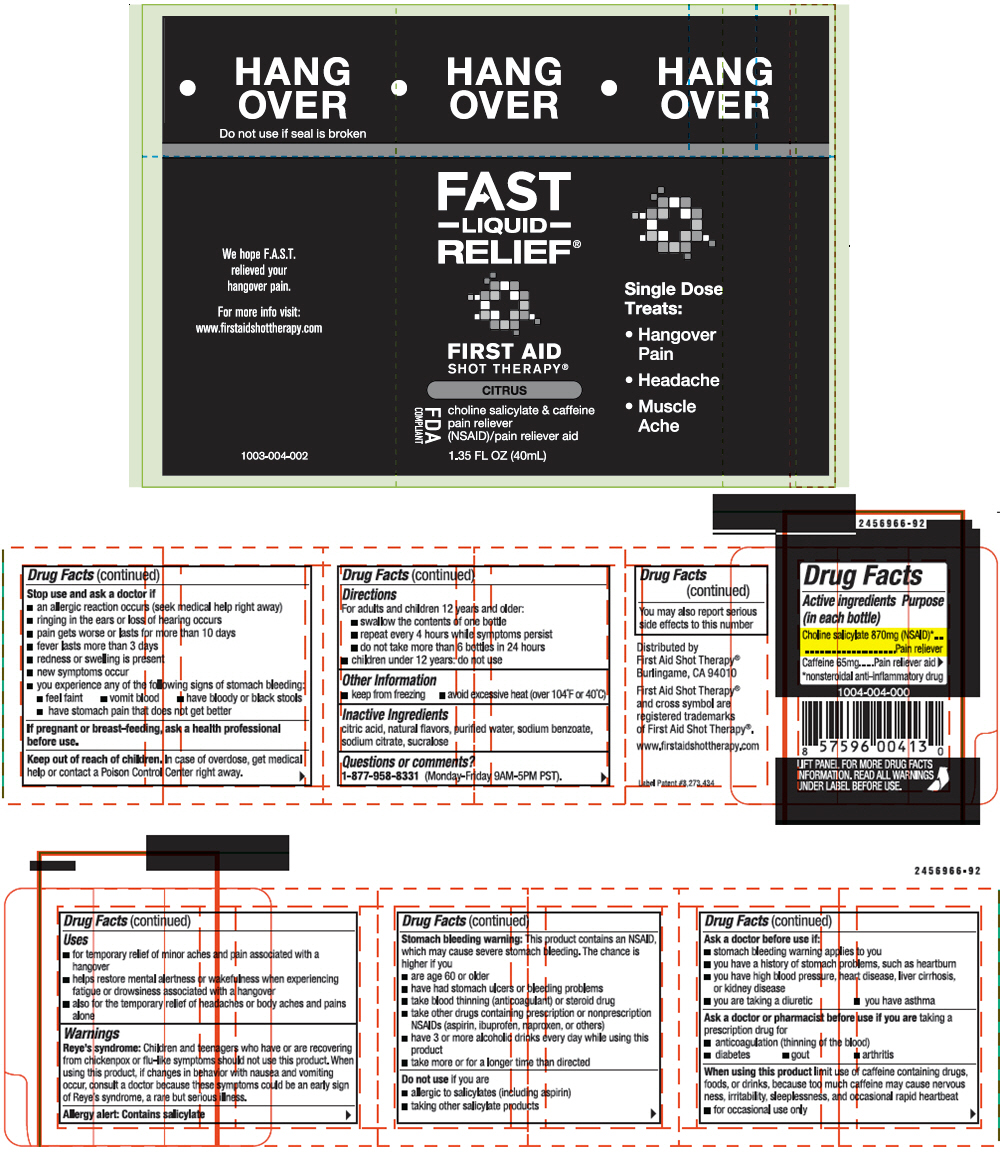 DRUG LABEL: First Aid Shot Therapy Hangover Relief
NDC: 57815-041 | Form: SOLUTION
Manufacturer: First Aid Beverages, Inc.
Category: otc | Type: HUMAN OTC DRUG LABEL
Date: 20150604

ACTIVE INGREDIENTS: Choline Salicylate 870 mg/40 mL; Caffeine 65 mg/40 mL
INACTIVE INGREDIENTS: Anhydrous Citric Acid; Sodium Benzoate; Sodium Citrate; Sucralose; Water

First Aid Shot Therapy® Hangover Relief

Drug Facts

ACTIVE INGREDIENT

PURPOSE

Active ingredients | Purposes (in each bottle)
Choline salicylate 870mg (NSAID) [nonsteroidal anti-inflammatory drug] | Pain reliever
Caffeine 65mg | Pain reliever aid

Uses

- for temporary relief of minor aches and pain associated with a hangover
- helps restore mental alertness or wakefulness when experiencing fatigue or drowsiness associated with a hangover
- also for temporary relief of headaches or body aches and pains alone

Warnings

Reye's syndrome

Children and teenagers who have or are recovering from chickenpox or flu-like symptoms should not use this product. When using this product, if changes in behavior with nausea and vomiting occur, consult a doctor because these symptoms could be an early sign of Reye's syndrome, a rare but serious illness.

Allergy alert

Contains salicylate

Stomach bleeding warning

This product contains an NSAID, which may cause severe stomach bleeding. The chance is higher if you

- are age 60 or older
- have had stomach ulcers or bleeding problems
- take blood thinning (anticoagulant) or steroid drug
- take other drugs containing prescription or nonprescription NSAIDs (aspirin, ibuprofen, naproxen, or others)
- have 3 or more alcoholic drinks every day while using this product
- take more or for a longer time than directed

Do not use if you are

- allergic to salicylates (including aspirin)
- taking other salicylate products

Ask a doctor before use if

- stomach bleeding warning applies to you
- you have a history of stomach problems, such as heartburn
- you have high blood pressure, heart disease, liver cirrhosis, or kidney disease
- you are taking a diuretic
- you have asthma

Ask a doctor or pharmacist before use if you are taking a prescription drug for

- anticoagulation (thinning of the blood)
- diabetes
- gout
- arthritis

When using this product limit use of caffeine containing drugs, foods, or drinks, because too much caffeine may case nervousness, irritability, sleeplessness, and occasional rapid heartbeat

- for occasional use only

Stop use and ask a doctor if

- an allergic reaction occurs (seek medical help right away)
- ringing in the ears or loss of hearing occurs
- pain gets worse or lasts for more than 10 days
- fever lasts more than 3 days
- redness or swelling is present
- new symptoms occur
- you experience any of the following signs of stomach bleeding
  - feel faint
  - vomit blood
  - have bloody or black stools
  - have stomach pain that does not get better

PREGNANCY OR BREAST FEEDING

If pregnant or breast-feeding, ask a health professional before use.

Keep out of reach of children. In case of overdose, get medical help or contact a Poison Control Center right away.

Directions

For adults and children 12 years or older:

- swallow the contents of one bottle
- repeat every 4 hours while symptoms persist
- do not take more than 6 bottles in 24 hours
- children under 12 years: do not use

Other Information

- Keep from freezing
- Avoid excessive heat (over 104°F or 40°C)

Inactive Ingredients

Citric acid, natural flavors, purified water, sodium benzoate, sodium citrate, sucralose

Questions or comments?

1-877-958-8331 (Monday-Friday 9AM-5PM PST)

PRINCIPAL DISPLAY PANEL - 40 mL Bottle Label

●
HANG
OVER

FAST
– LIQUID –
RELIEF®

FIRST AID
SHOT THERAPY®

CITRUS

choline salicylate & caffeine
pain reliever
(NSAID)/pain reliever aid

1.35 FL OZ (40mL)

FDA
COMPLIANT